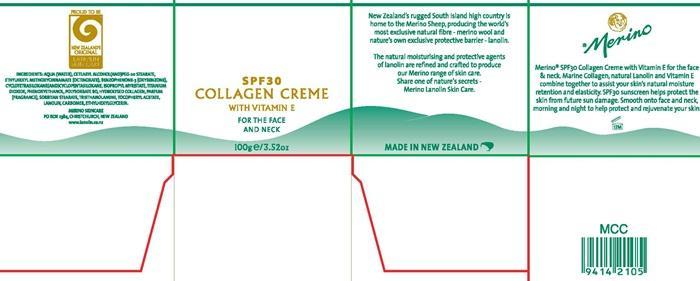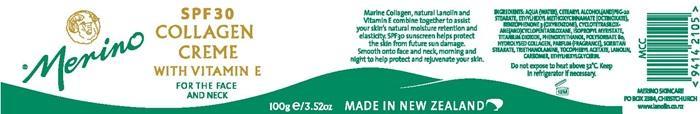 DRUG LABEL: Merino Collagen SPF 30
NDC: 34834-003 | Form: CREAM
Manufacturer: Merino Lanolin Skin Care Products
Category: otc | Type: HUMAN OTC DRUG LABEL
Date: 20141114

ACTIVE INGREDIENTS: OCTINOXATE 7.5 g/100 g; OXYBENZONE 4 g/100 g
INACTIVE INGREDIENTS: WATER; CETOSTEARYL ALCOHOL; PEG-20 STEARATE; CYCLOMETHICONE 4; CYCLOMETHICONE 5; ISOPROPYL MYRISTATE; TITANIUM DIOXIDE; PHENOXYETHANOL; POLYSORBATE 80; MARINE COLLAGEN, SOLUBLE; SORBITAN MONOSTEARATE; TROLAMINE; .ALPHA.-TOCOPHEROL ACETATE; LANOLIN ; CARBOMER HOMOPOLYMER TYPE C (ALLYL PENTAERYTHRITOL CROSSLINKED); ETHYLHEXYLGLYCERIN

Ingredients

ETHYLHEXYL METHOXYCINNAMATE (OCTINOXATE)
BENZOPHENONE 3 (OXYBENZONE)

Purpose

helps protect the skin from future sun damage

Keep out of reach of children

Enter section text here

Uses

Assist your skin's natural moisture retention and elasticity. SPF 30 sunscreen helps protect the skin from future sun damage.

Warnings

Do not expose to heat above 30° C.

Keep in refrigerator if necessary

Directions

Smooth onto face and neck, morning and night to help protect and rejuvenate your skin.

Ingregients

AQUA (WATER), CETEARYL ALCOHOL (AND) PEG-20 STEARATE, CYCLOTETRASILOXANE (AND) CYCLOPENTASILOXANE, ISOPROPYL MYRISTATE, TITANIUM DIOXIDE, PHENOXYETHANOL, POLYSORBATE 80, HYDROLYSED COLLAGEN, PARFUM (FRAGRANCE), SORBITAN STEARATE, TRIETHANOLAMINE, TOCOPHERYL ACETATE, LANOLIN, CARBOMER, ETHYLHEXYLGLYCERIN

Product Label

Merino

SPF 30 COLLAGEN CREME
WITH VITAMIN E

FOR THE FACE AND NECK
100 g e/ 3.52 oz

MADE IN NEW ZEALAND

Marine Collagen, natural Lanolin and Vitamin E combine together to assist your skin's natural moisture retention and elasticity.

New Zealand's rugged South Island high country is home to the Merino Sheep, producing the world's most exclusive natural fibre - merino wool and nature's own exclusive protective barrier - lanolin.

The natural moisturising and protective agents of lanolin are refined and crafted to produce our Merino range of skin care. Share one nature's secrets - Merino Lanolin Skin Care.

MERINO SKINCARE
P.O. BOX 2384, CHRISTCHURCH

www.lanolin.co.nz